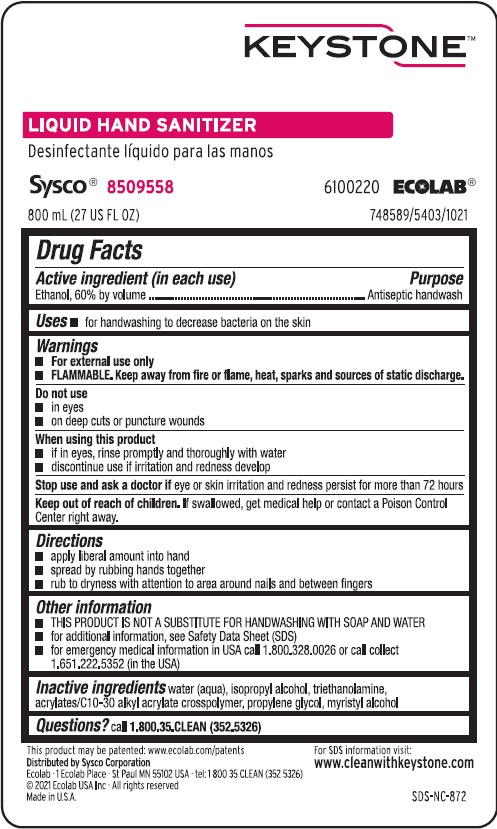 DRUG LABEL: Keystone Liquid Hand Sanitizer
NDC: 47593-466 | Form: SOLUTION
Manufacturer: Ecolab Inc.
Category: otc | Type: HUMAN OTC DRUG LABEL
Date: 20251216

ACTIVE INGREDIENTS: ALCOHOL 60 mL/100 mL
INACTIVE INGREDIENTS: WATER; ISOPROPYL ALCOHOL; TROLAMINE; CARBOMER COPOLYMER TYPE B (ALLYL PENTAERYTHRITOL CROSSLINKED); PROPYLENE GLYCOL; MYRISTYL ALCOHOL

Drug Facts

Active ingredient (in each use)

Ethanol, 60% by volume

Purpose

Antiseptic handwash

Uses

- for handwashing to decrease bacteria on the skin

Warnings

- For external use only
- FLAMMABLE. Keep away from fire or flame, heat, sparks and sources of static discharge.

Do not use

- in eyes
- on deep cuts or puncture wounds

When using this product

- If in eyes, rinse promptly and thoroughly with water
- Discontinue use if irritation and redness develop

Stop use and ask a doctor if

eye or skin irritatin and redness persist for more than 72 hours

Keep out of reach of children. If swallowed, get medical help or contact a Poison Control Center right away.

Directions

- apply liberal amount into hand
- spread by rubbing hands together
- rub to dryness with attention to area around nails and between fingers

Other information

- THIS PRODUCT IS NOT A SUBSTITUTE FOR HANDWASHING WITH SOAP AND WATER
- For additional information, see Safety Data Sheet (SDS)
- For emergency medical information in the USA call 1.800.328.0026 or call collect 1.651.222.5352 (in the USA)

INACTIVE INGREDIENT

Inactive ingredients water (aqua), isopropyl alcohol, triethanolamine, acrylates/C10-C30 alkyl acrylate crosspolymer, propylene glycol, myristyl alcohol

Questions? call 1-800-35-CLEAN (352-5326)

Principal Display Panel and Representative Label

Keystone

Liquid Hand Sanitizer

Sysco 8509558 6100220 ECOLAB

800 mL (27 US FL OZ) 748589/5403/1021

Distributed by Sysco Corporation

Ecolab - 1 Ecolab Place - St. Paul, MN 55102 USA - tel. 1 800 352 5326

©2021Ecolab USA Inc. - All rights reserved

Made in U.S.A. SDS-NC-872